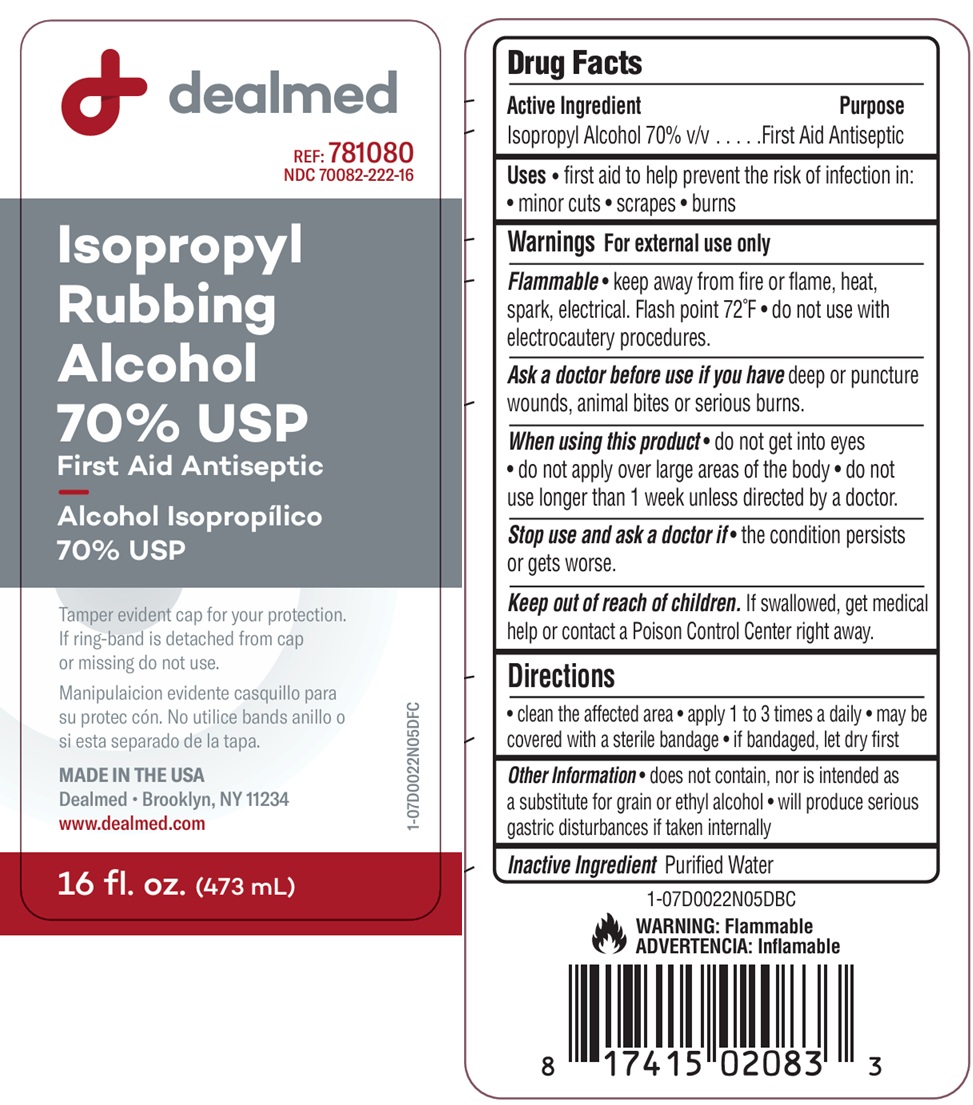 DRUG LABEL: Isopropyl Rubbing Alcohol
NDC: 70082-222 | Form: SOLUTION
Manufacturer: DealMed Medical Supplies LLC
Category: otc | Type: HUMAN OTC DRUG LABEL
Date: 20260113

ACTIVE INGREDIENTS: ISOPROPYL ALCOHOL 70 mL/100 mL
INACTIVE INGREDIENTS: WATER

Isopropyl Alcohol 70% USP

Drug Facts

Active Ingredient

Isopropyl Alcohol 70% v/v

Purpose

First Aid Antiseptic

Uses

First aid to help prevent the risk of infection in: minor cuts, scrapes, burns

Warnings

For external use only

Flammable

Keep away from fire or flame, heat, spark, electrical. Flash point 72ºF

Do not use with electrocautery procedures

Ask a doctor before use if you have deep or puncture wounds, animal bites or serious burns

When using this product

do not get into eyes

do ot apply over large areas of the body

do not use longer than 1 week unless directed by a doctor

Stop use and ask a doctor if condition persists or gets worse

Keep out of reach of children.

If swallowed, get medical help or contact a Poison Control Center right away

Directions

• clean the affected area

• apply 1 to 3 times a daily

• may be covered with a sterile bandage

• if bandaged, let dry first

Other Information

Does not contain, nor is intended as a substitute for grain or ethyl alcohol

Will produce serious gastric disturbances if taken internally

Inactive Ingredient

purified water